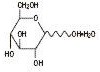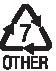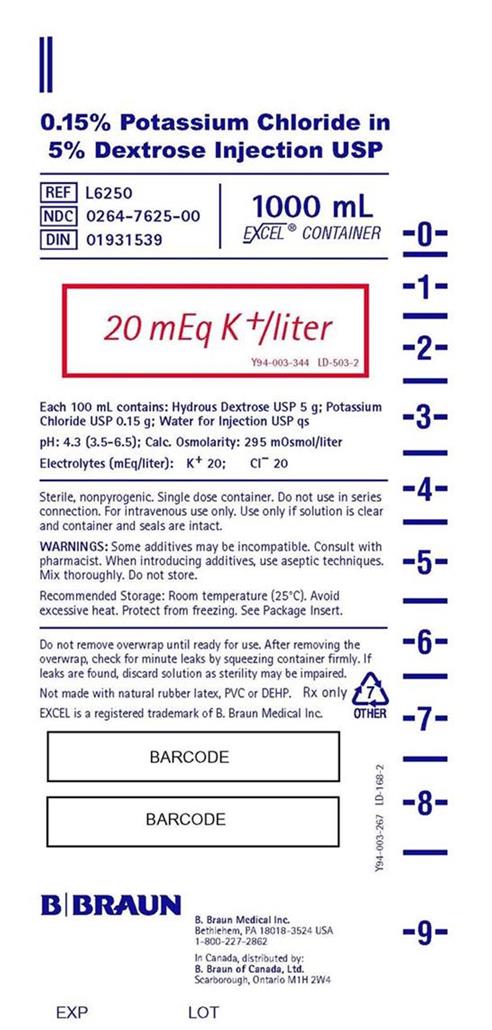 DRUG LABEL: POTASSIUM CHLORIDE IN DEXTROSE
NDC: 0264-7625 | Form: SOLUTION
Manufacturer: B. Braun Medical Inc.
Category: prescription | Type: HUMAN PRESCRIPTION DRUG LABEL
Date: 20200731

ACTIVE INGREDIENTS: DEXTROSE 5 g/100 mL; POTASSIUM CHLORIDE 0.15 g/100 mL
INACTIVE INGREDIENTS: WATER

HIGHLIGHTS OF PRESCRIBING INFORMATION

These highlights do not include all the information needed to use POTASSIUM CHLORIDE IN DEXTROSE INJECTION safely and effectively. See full prescribing information for POTASSIUM CHLORIDE IN DEXTROSE INJECTION.
POTASSIUM CHLORIDE IN DEXTROSE injection, for intravenous use
Initial U.S. Approval: 1979

RECENT MAJOR CHANGES

Contraindications (4) 07/2020

Warnings and Precautions (5.1, 5.2, 5.3, 5.4, 5.5, 5.6, 5.7) 07/2020

1 INDICATIONS AND USAGE

Potassium Chloride in Dextrose Injection is indicated as a source of electrolytes, calories, and water for hydration.

2 DOSAGE AND ADMINISTRATION

- Only for intravenous infusion. (2.1, 5.2)
- See full prescribing information for information on preparation, administration, dosing considerations and instructions for use. (2.1, 2.2, 2.3)

3 DOSAGE FORMS AND STRENGTHS

Injection: 20 mEq Potassium Chloride in 5% Dextrose Injection, USP in a 1000 mL plastic container.

4 CONTRAINDICATIONS

- known hypersensitivity to potassium chloride and/or dextrose (5.1)
- clinically significant hyperkalemia (5.2)
- clinically significant hyperglycemia (5.3)

5 WARNINGS AND PRECAUTIONS

- Hypersensitivity Reactions: monitor for signs and symptoms and discontinue infusion if reactions occur. (5.1)
- Hyperkalemia: May result in cardiac arrhythmias. Avoid use in patients with, or at risk for, hyperkalemia. If use cannot be avoided, use a product with a low amount of potassium chloride, infuse slowly and monitor serum potassium concentrations and ECGs. (5.2)
- Hyperglycemia or Hyperosmolar Hyperglycemic State: Monitor blood glucose and administer insulin as needed. (5.3, 8.4)
- Hyponatremia: Avoid in patients with or at risk for hyponatremia. If use cannot be avoided, monitor serum sodium concentrations. (5.4, 8.4)
- Hypokalemia: Avoid in patients with or at risk for hypokalemia. If use cannot be avoided, monitor serum potassium levels. (5.5)
- Fluid Overload: Avoid in patients with or at risk for fluid and/or solute overloading. If use cannot be avoided, monitor daily fluid balance and electrolyte, concentrations and acid-base balance, as needed and especially during prolonged use. (5.6)
- Refeeding Syndrome: Monitor severely undernourished patients and slowly increase nutrient intake. (5.7)

6 ADVERSE REACTIONS

Adverse reactions include electrolyte imbalances, hyperglycemia, and hypervolemia and injection site reactions.

To report SUSPECTED ADVERSE REACTIONS, contact B. Braun Medical Inc. at 1-866-854-6851 or FDA at 1-800-FDA-1088 or www.fda.gov/medwatch.

7 DRUG INTERACTIONS

- Other Products that Cause Hyperkalemia: Avoid use in patients receiving such products. If use cannot be avoided, monitor serum potassium concentrations. (7.1)
- Other Products that Affect Glycemic Control, Vasopressin or Fluid and/or Electrolyte Balance: Monitor blood glucose concentrations, fluid balance serum electrolyte concentrations and acid-base balance. (7.2)

FULL PRESCRIBING INFORMATION

1 INDICATIONS AND USAGE

Potassium Chloride in Dextrose Injection is indicated as a source of electrolytes, calories, and water for hydration.

2 DOSAGE AND ADMINISTRATION

2.1 Important Administration Instructions

- Potassium Chloride in Dextrose Injection is only for intravenous infusion [see Warnings and Precautions (5.2)].
- For patients receiving Potassium Chloride in Dextrose Injection at greater than maintenance rates, frequent monitoring of serum potassium concentrations and serial electrocardiograms (ECGs) are recommended.
- The osmolarity of Potassium Chloride in Dextrose Injection is 295 mOsmol/L (calc). Peripheral administration is generally acceptable; however; consider central vein administration if there is peripheral vein irritation, phlebitis, and/or associated pain.
- Do not administer Potassium Chloride in Dextrose Injection simultaneously with blood products through the same administration set because of the possibility of pseudo agglutination or hemolysis.
- To prevent air embolism, use a non-vented infusion set or close the vent on a vented set, avoid multiple connections, do not connect flexible containers in series, fully evacuate residual gas in the container prior to administration, do not pressurize the flexible container to increase flow rates, and if administration is controlled by a pumping device, turn off pump before the container runs dry.
- Prior to infusion, visually inspect the solution for particulate matter. The solution should be clear and there should be no precipitates. Do not administer unless solution is clear and container is undamaged.
- Use of a final filter is recommended during administration of parenteral solutions, where possible.

2.2 Recommended Dosage

The infusion rate and volume depends on the age, weight, clinical and metabolic conditions of the patient and concomitant therapy. Electrolyte supplementation may be indicated according to the clinical needs of the patient.

The administration rate should be governed, especially for premature infants with low birth weight, during the first few days of therapy, by the patient’s tolerance to dextrose. Increase the infusion rate gradually as indicated by frequent monitoring of blood glucose concentrations [see Warnings and Precautions (5.1), Use in Specific Populations (8.4)].

2.3 Instructions for Use

To Open

- Tear overwrap down at notch and remove solution container.
- Visually inspect the container. The closure system has two ports; the one for the administration set has a tamper evident plastic protector and the other is a medication addition site. Evaluate the following:
- Read the label. Ensure solution is the one ordered and is within the expiration date.
- If the outlet port protector is damaged, detached or not present, discard container.
- Invert the container and check to ensure the solution is clear and there is no haze or particulate matter. Discard if there is a color change and/or the appearance of precipitates, insoluble complexes or crystals.
- Check for minute leaks by squeezing solution container firmly. If leaks are found, discard solution as sterility may be impaired.
- If supplemental medication is desired, follow directions below before preparing for administration.

Preparation for Administration

1. Remove plastic protector from sterile set port at bottom of container.
2. Attach administration set. Refer to complete directions accompanying set.

To Add Medication

- Additives may be incompatible. Complete information is not available. Do not use additives known or determined to be incompatible.
- Before adding a substance or medication, verify that it is soluble and/or stable in Potassium Chloride in Dextrose Injection and that the pH range of Potassium Chloride in Dextrose Injection is appropriate.
- Consult with pharmacist, if available. If, in the informed judgment of the healthcare provider, it is deemed advisable to introduce additives, use aseptic technique.

To Add Medication Before Solution Administration

1. Prepare medication site.
2. Using syringe with 18-22 gauge needle, puncture medication port and inner diaphragm and inject.
3. Squeeze and tap ports while ports are upright and mix solution and medication thoroughly.
4. After addition, check to ensure the solution is clear and there are no precipitates. Discard if there is a color change and/or the appearance of precipitates, insoluble complexes or crystals.

To Add Medication During Solution Administration

1. Close clamp on the set.
2. Prepare medication site.
3. Using syringe with 18-22 gauge needle of appropriate length (at least 5/8 inch), puncture resealable medication port and inner diaphragm and inject.
4. Remove container from IV pole and/or turn the container so the ports are in an upright position.
5. Evacuate both ports by tapping and squeezing them while container ports are in the upright position.
6. Mix solution and medication thoroughly.
7. After addition, check to ensure the solution is clear and there are no precipitates. Discard if there is a color change and/or the appearance of precipitates, insoluble complexes or crystals, do not use.
8. Return container to in use position and continue administration.

Storage

- Use promptly; do not store solutions containing additives.
- Single-dose container.
- Discard any unused portion

3 DOSAGE FORMS AND STRENGTHS

Potassium Chloride in 5% Dextrose Injection USP is supplied sterile and nonpyrogenic in 1000 mL single-dose, flexible container.

4 CONTRAINDICATIONS

Potassium Chloride in Dextrose Injection is contraindicated in patients with:

- known hypersensitivity to potassium chloride and/or dextrose [see Warnings and Precautions 5.1)]
- clinically significant hyperkalemia [see Warnings and Precautions (5.2)]
- clinically significant hyperglycemia [see Warnings and Precautions (5.3)]

5 WARNINGS AND PRECAUTIONS

5.1 Hypersensitivity Reactions

Hypersensitivity and infusion reactions, including anaphylaxis, have been reported with Potassium Chloride in Dextrose Injection [see Adverse Reactions (6)]. Stop the infusion immediately if signs or symptoms of a hypersensitivity or infusion reaction develops [see Contraindications (4)]. Appropriate therapeutic countermeasures must be instituted as clinically indicated.

5.2 Hyperkalemia

Potassium-containing solutions, including Potassium Chloride in Dextrose Injection may increase the risk of hyperkalemia. Hyperkalemia can be asymptomatic and manifest only by increased serum potassium concentrations and/or characteristic electrocardiographic (ECG) changes. Cardiac arrhythmias, some fatal, can develop at any time during hyperkalemia.

To avoid life threatening hyperkalemia, do not administer Potassium Chloride in Dextrose Injection as an intravenous push (i.e., intravenous injection manually with a syringe connected to the intravenous access, without quantitative infusion device [see Dosage and Administration (2.1)].

Patients at increased risk of developing hyperkalemia and cardiac arrhythmias include those:

- with severe renal impairment, acute dehydration, extensive tissue injury or burns, and certain cardiac disorders such as congestive heart failure or AV block (especially if they receive digoxin).
- with hyperosmolality, acidosis, or undergoing correction of alkalsis (conditions associated with a shift of potassium from intracellular to extracellular space).
- treated concurrently or recently with agents or products that can cause or increase the risk of hyperkalemia [see Drug Interactions (7.1)].

Avoid use of Potassium Chloride in 5% Dextrose Injection in patients with, or at risk for, hyperkalemia. If use cannot be avoided, use a product with a low amount of potassium chloride, infuse slowly and monitor serum potassium concentrations and ECGs.

5.3 Hyperglycemia and Hyperosmolar Hyperglycemic State

The use of dextrose infusions in patients with impaired glucose tolerance (such as diabetes mellitus, renal impairment, or in the presence of sepsis, trauma, or shock) may worsen hyperglycemia. Administration of dextrose at a rate exceeding the patient’s utilization rate may lead to hyperglycemia, coma, and death.

Hyperglycemia is associated with an increase in serum osmolality, resulting in osmotic diuresis, dehydration and electrolyte losses [see Warnings and Precautions (5.6)]. Patients with underlying central nervous system disease and renal impairment who receive dextrose infusions, may be at greater risk of developing hyperosmolar hyperglycemic state.

Monitor blood glucose concentrations and treat hyperglycemia to maintain concentrations within normal limits while administering Potassium Chloride in Dextrose Injection. Insulin may be administered or adjusted to maintain optimal blood glucose concentrations.

5.4 Hyponatremia

Potassium Chloride in 5% Dextrose Injection is an isotonic solution [see Description, Table 1 (11)]. In the body, however, glucose containing fluids can become extremely physiologically hypotonic due to rapid glucose metabolization. Monitoring of serum sodium is particularly important for hypotonic fluids.

Depending on the tonicity of the solution, the volume and rate of infusion, and depending on a patient’s underlying clinical condition and capability to metabolize glucose, intravenous administration of glucose can cause electrolyte disturbances, most importantly hypo- or hyperosmotic hyponatremia.

The risk for hyponatremia is increased, in pediatric patients, elderly patients, postoperative patients, those with psychogenic polydipsia and in patients treated with medications that increase the risk of hyponatremia (such as certain diuretic, antiepileptic and psychotropic medications). Close clinical monitoring may be warranted.

Acute hyponatremia can lead to acute hyponatremic encephalopathy characterized by headache, nausea, seizures, lethargy and vomiting. Patients with brain edema are at particular risk of severe, irreversible and life-threatening brain injury. Patients at increased risk for developing complications of hyponatremia, such as hyponatremic encephalopathy include pediatric patients; women, in particular, premenopausal women; patients with hypoxemia; and in patients with underlying central nervous system disease [see Use in Specific Populations (8.4, 8.5)].

Rapid correction of hyponatremia is potentially dangerous with risk of serious neurologic complications such as osmotic demyelination syndrome with risk of seizures and cerebral edema. To avoid complications, monitor serum sodium and chloride concentrations, fluid status, acid-base balance, and signs of neurologic complications.

High volume infusion must be used with close monitoring in patients with cardiac or pulmonary failure, and in patients with non-osmotic vasopressin release (including SIADH), due to the risk of hospital- acquired hyponatremia.

5.5 Hypokalemia

The infusion of solutions with Potassium Chloride in 5% Dextrose Injection, USP may result in hypokalemia, leading to arrhythmias, muscle weakness, paralysis, heart block, and rhabdomyolysis.

Hypokalemic periodic paralysis, metabolic alkalosis, increased gastrointestinal losses (e.g., diarrhea, vomiting), prolonged low potassium diet or primary hyperaldosteronism may increase the risk of hypokalemia. If use cannot be avoided, monitor serum potassium levels.

5.6 Fluid Overload

Depending on the volume and rate of infusion, the patient’s underlying clinical condition and capability to metabolize dextrose, intravenous administration of Potassium Chloride in 5% Dextrose and Sodium Chloride Injection can cause fluid and/or solute overloading resulting in dilution of serum electrolyte concentrations, overhydration, congested states or pulmonary edema.

Avoid Potassium Chloride in Dextrose Injection in patients with or at risk for fluid and/or solute overloading. If use cannot be avoided, monitor fluid balance, electrolyte concentrations, and acid-base balance as needed and especially during prolonged use.

5.7 Refeeding syndrome

Refeeding severely undernourished patients may result in the refeeding syndrome that is characterized by the shift of potassium, phosphorus, and magnesium intracellularly as the patient becomes anabolic. Thiamine deficiency and fluid retention may also develop. To prevent these complications, monitor severely undernourished patients and slowly increasing nutrient intake.

6 ADVERSE REACTIONS

The following adverse reactions associated with the use of Potassium Chloride in Dextrose Injection were identified in post marketing reports. Because these reactions were reported voluntarily from a population of uncertain size, it is not always possible to reliably estimate their frequency or establish a causal relationship to drug exposure.

The following clinically significant adverse reactions are described elsewhere in the labeling:

- Hypersensitivity reactions: including anaphylaxis and chills [see Warnings and Precautions (5.1)]
- Hyperkalemia, including cardiac arrest, as a manifestation [see Warnings and Precautions (5.2)]
- Hyponatremia and hyponatremic encephalopathy [see Warnings and Precautions (5.4)]
- Hypokalemia [see Warnings and Precautions (5.5)]
- Hypervolemia [see Warnings and Precautions (5.6)]
- Injection site reactions: infection at the site of injection, venous thrombosis or phlebitis extending from the site of injection, extravasation, infusion site rash, infusion site pain, infusion site vesicles, infusion site pruritus, pyrexia and chills

7 DRUG INTERACTIONS

7.1 Other Products that Cause Hyperkalemia

Administration of Potassium Chloride in Dextrose Injection in patients treated concurrently or recently with other products that can cause hyperkalemia or increase the risk of hyperkalemia (e.g., potassium-sparing diuretics, angiotensin-converting enzyme inhibitors, angiotensin receptor blockers) increases the risk of severe and potentially fatal hyperkalemia, in particular in the presence of other risk factors for hyperkalemia [see Warnings and Precautions (5.2)]. Avoid use of Potassium Chloride in 5% Dextrose Injection in patients receiving such products. If use cannot be avoided, monitor serum potassium concentrations.

7.2 Other Products that Affect Glycemic Control, Vasopressin or Fluid and/or Electrolyte Balance

Potassium Chloride in Dextrose Injection can affect glycemic control, vasopressin and fluid and/or electrolyte balance [see Warnings and Precautions (5.3, 5.4, 5.5, 5.6)]. Monitor blood glucose concentrations, fluid balance, serum electrolyte concentrations and acid-base balance when using Potassium Chloride in Dextrose Injection in patients treated with other substances that affect glycemic control, vasopressin or fluid and/or electrolyte balance.

8 USE IN SPECIFIC POPULATIONS

8.1 Pregnancy

Risk Summary

Appropriate administration of Potassium Chloride in Dextrose Injection during pregnancy is not expected to cause adverse developmental outcomes, including congenital malformations. Animal reproduction studies have not been conducted with Potassium Chloride in Dextrose Injection.

The estimated background risk of major birth defects and miscarriage for the indicated population is unknown. All pregnancies have a background risk of birth defect, loss, or other adverse outcomes. In the U.S. general population, the estimated background risk of major birth defects and miscarriage in clinically recognized pregnancies is 2 to 4% and 15 to 20%, respectively.

8.2 Lactation

Risk Summary

Potassium is present in human breast milk. There are no data on the effects of Potassium Chloride in Dextrose Injection on a breastfed infant or the effects on milk production.

The developmental and health benefits of breastfeeding should be considered along with the mother’s clinical need for Potassium Chloride in Dextrose Injection and any potential adverse effects on the breastfed infant from Potassium Chloride in Dextrose Injection or from the underlying maternal condition.

8.4 Pediatric Use

The safety profile of Potassium Chloride in Dextrose Injection in pediatric patients is similar to adults.

Neonates, especially premature infants with low birth weight, are at increased risk of developing hypo- or hyperglycemia and therefore need close monitoring during treatment with intravenous glucose solutions to ensure adequate glycemic control in order to avoid potential long term adverse effects.

Closely monitor plasma electrolyte concentrations in pediatric patients who may have impaired ability to regulate fluids and electrolytes. In very low birth weight infants, excessive or rapid administration of Potassium Chloride in Dextrose Injection may result in increased serum osmolality and risk of intracerebral hemorrhage.

Children (including neonates and older children) are at increased risk of developing hyponatremia as well as for developing hyponatremic encephalopathy.

8.5 Geriatric Use

Potassium Chloride in Dextrose Injection is known to be substantially excreted by the kidney, and the risk of adverse reactions to this product may be greater in patients with impaired renal function [see Warnings and Precautions (5.2, 5.3)].

Elderly patients are at increased risk of developing hyponatremia as well as for developing hyponatremic encephalopathy [see Warnings and Precautions (5.4)].

Dose selection for an elderly patient should be cautious, starting at the low end of the dosing range, reflecting the greater frequency of decreased hepatic, renal, or cardiac function, and of concomitant disease or other drug therapy.

8.6 Renal Impairment

Administration of Potassium Chloride in Dextrose Injection in patients with renal impairment may result in hyperkalemia, hyponatremia, and/or fluid overload. Monitor patients with renal impairment for development of these adverse reactions [see Warnings and Precautions (5.2, 5.4, 5.6)].

10 OVERDOSAGE

Excess administration of Potassium Chloride in Dextrose Injection can cause:

Hyperkalemia

Manifestations of hyperkalemia may include:

- disturbances in cardiac conduction and arrhythmias, including bradycardia, heart block, asystole, ventricular tachycardia, ventricular fibrillation, and ECG changes (peaking of T waves, loss of
  P waves, and QRS widening)
- hypotension
- muscle weakness up to and including muscular and respiratory paralysis, paresthesia
  of extremities
- gastrointestinal symptoms (ileus, nausea, vomiting, abdominal pain)

The presence of any ECG findings that are suspected to be caused by hyperkalemia should be considered a medical emergency.

If hyperkalemia is present or suspected, discontinue the infusion immediately and institute close ECG, laboratory and other monitoring and, as necessary, corrective therapy to reduce serum potassium concentrations [see Warnings and Precautions (5.2)].

Other Electrolyte and Fluid Disorders

- Hyperglycemia, hyperosmolality, and adverse effects on water and electrolyte balance, and corresponding complications, which can be fatal [see Warnings and Precautions (5.3, 5.6)].
- Hyponatremia, manifestations may include seizures, coma, cerebral edema and death)
  [see Warnings and Precautions (5.4)].
- Fluid overload (which can lead to central and/or peripheral edema) [see Warnings and Precautions (5.6)].
- Hypernatremia, especially in patients with severe renal impairment.

Interventions include discontinuation of the infusion, dose reduction, monitoring of fluid balance, electrolyte concentrations and acid-base balance and institution of appropriate corrective measures such as administration of exogenous insulin.

11 DESCRIPTION

(See chart below for quantitative information.)

Potassium Chloride in 5% Dextrose Injection USP is sterile, nonpyrogenic solution for fluid and electrolyte replenishment and caloric supply. It contains no bacteriostatic or antimicrobial agents. This product is intended for intravenous administration.

The formulas of the active ingredients are:

Ingredients | Molecular Formula | Molecular Weight
Potassium Chloride USP | KCl | 74.55
Hydrous Dextrose USP |  | 198.17

Composition – Each 100 mL contains: |  |  | Concentration of Electrolytes (mEq/liter) |  | Calories per liter | Calculated Osmolarity mOsmol/liter | pH
Solution | Hydrous Dextrose USP | Potassium Chloride USP | Concentration of Electrolytes (mEq/liter) |  | Calories per liter | Calculated Osmolarity mOsmol/liter | pH
Solution | Hydrous Dextrose USP | Potassium Chloride USP | Potassium | Chloride | Calories per liter | Calculated Osmolarity mOsmol/liter | pH
0.15% Potassium Chloride in 5% Dextrose Injection USP | 5 g | 0.15 g | 20 | 20 | 170 | 295 | 4.3 (3.5-6.5)
Water for Injection USP qs

Dextrose is derived from corn.

The plastic container is made from a multilayered film specifically developed for parenteral drugs. It contains no plasticizers and exhibits virtually no leachables. The solution contact layer is a rubberized copolymer of ethylene and propylene. The container is nontoxic and biologically inert. The container-solution unit is a closed system and is not dependent upon entry of external air during administration. The container is overwrapped to provide protection from the physical environment and to provide an additional moisture barrier when necessary.

12 CLINICAL PHARMACOLOGY

12.1 Mechanism of Action

Potassium Chloride in Dextrose Injection is a source of water, electrolytes and calories. It is capable of inducing diuresis depending on the clinical condition of the patient.

16 HOW SUPPLIED/STORAGE AND HANDLING

Potassium Chloride in 5% Dextrose Injection USP is supplied sterile and nonpyrogenic in 1000 mL EXCEL® Containers packaged 12 per case.

REF | Size | NDC | mEq Potassium | Product Name
L6250 | 1000 mL | 0264-7625-00; (Canada DIN 01931539) | 20 mEq | Potassium Chloride in 5% Dextrose Injection, USP

Not made with natural rubber latex, PVC or DEHP.

Storage

Avoid excessive heat. Protect from freezing. Store at room temperature (25°C); brief exposure up to 40°C does not adversely affect the product.

Storage in automated dispensing machines: Brief exposure up to 2 weeks to ultraviolet or fluorescent light does not adversely affect the product labeling legibility; prolonged exposure can cause fading of the red label. Rotate stock frequently.

17 PATIENT COUNSELING INFORMATION

Inform patients, caregivers or home healthcare providers of the following risks of Potassium Chloride in Dextrose Injection:

- Hypersensitivity reactions [see Warnings and Precautions (5.1)]
- Hyperkalemia [see Warnings and Precautions (5.2)]
- Hyperglycemia and hyperosmolar hyperglycemic state [see Warnings and Precautions (5.3)]
- Hyponatremia [see Warnings and Precautions (5.4)]
- Hypokalemia [see Warnings and Precautions (5.5)]
- Fluid overload [see Warnings and Precautions (5.6)]
- Refeeding syndrome [see Warnings and Precautions (5.7)]

Rx Only

EXCEL is a registered trademark of B. Braun Medical Inc.

B. Braun Medical Inc.
Bethlehem, PA 18018-3524 USA
1-800-227-2862

In Canada, distributed by:
B. Braun of Canada, Ltd.
Scarborough, Ontario M1H 2W4

Y36-002-975 LD-235-3

PRINCIPAL DISPLAY PANEL - 1000 mL Container

0.15% Potassium Chloride in 5% Dextrose Injection USP

REF L6250

NDC 0264-7625-00

DIN 01931539

1000 mL
EXCEL® CONTAINER

20 mEq K+/liter

Y94-003-344 LD-503-2

Each 100 mL contains: Hydrous Dextrose USP 5 g; Potassium Chloride USP 0.15 g; Water for Injection USP qs

pH: 4.3 (3.5-6.5); Calc. Osmolarity: 295 mOsmol/liter

Electrolytes (mEq/liter): K^+ 20; Cl^– 20

Sterile, nonpyrogenic. Single dose container. Do not use in series connection. For intravenous use only. Use only if solution is clear and container and seals are intact.

WARNINGS: Some additives may be incompatible. Consult with pharmacist. When introducing additives, use aseptic techniques.
Mix thoroughly. Do not store.

Recommended Storage: Room temperature (25°C). Avoid excessive heat. Protect from freezing. See Package Insert.

Do not remove overwrap until ready for use. After removing the overwrap, check for minute leaks by squeezing container firmly. If leaks are found, discard solution as sterility may be impaired.

Not made with natural rubber latex, PVC or DEHP.

EXCEL is a registered trademark of B. Braun Medical Inc.

Rx only

B. Braun Medical Inc.
Bethlehem, PA 18018-3524 USA
1-800-227-2862

In Canada, distributed by:
B. Braun of Canada, Ltd.
Scarborough, Ontario M1H 2W4
Y94-003-267 LD-168-2

EXP
LOT